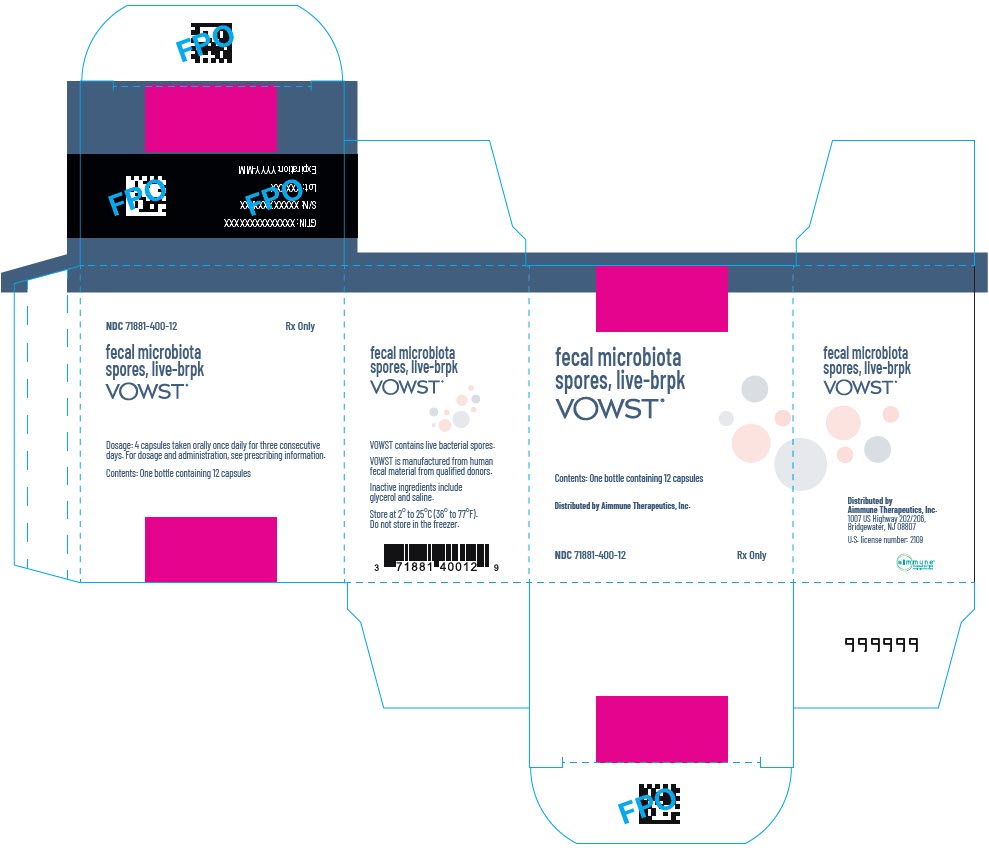 DRUG LABEL: VOWST
NDC: 71881-400 | Form: CAPSULE
Manufacturer: Aimmune Therapeutics, Inc.
Category: prescription | Type: HUMAN PRESCRIPTION DRUG LABEL
Date: 20250321

ACTIVE INGREDIENTS: DONOR HUMAN STOOL SPORES (ETHANOL TREATED) 30000000 [CFU]/1 1
INACTIVE INGREDIENTS: SODIUM CHLORIDE; WATER; GLYCERIN

HIGHLIGHTS OF PRESCRIBING INFORMATION

These highlights do not include all the information needed to use VOWST™ safely and effectively. See full prescribing information for VOWST.
VOWST (fecal microbiota spores, live-brpk) capsules, for oral administration
Initial U.S. Approval: 2023

1 INDICATIONS AND USAGE

VOWST is indicated to prevent the recurrence of Clostridioides difficile infection (CDI) in individuals 18 years of age and older following antibacterial treatment for recurrent CDI (rCDI). (1)

Limitation of Use:

VOWST is not indicated for treatment of CDI.

2 DOSAGE AND ADMINISTRATION

For oral administration only. (2)

- Prior to taking the first dose:
  - Complete antibacterial treatment for rCDI 2 to 4 days before initiating treatment with VOWST. (2.1)
  - Drink 296 mL (10 oz) of magnesium citrate on the day before and at least 8 hours prior to taking the first dose of VOWST. In clinical studies, participants with impaired kidney function received polyethylene glycol electrolyte solution (250 mL GoLYTELY, not approved for this use). (2.1)
- The dosage of VOWST is 4 capsules taken orally once daily for 3 consecutive days. (2.2)
- Take each dose (4 capsules) on an empty stomach prior to the first meal of the day. (2.2)

3 DOSAGE FORMS AND STRENGTHS

Capsule. A single dose is 4 capsules. (3)

4 CONTRAINDICATIONS

None. (4)

6 ADVERSE REACTIONS

Most common adverse reactions (reported in ≥5% of participants) were abdominal distension (31.1%), fatigue (22.2%), constipation (14.4%), chills (11.1%) and diarrhea (10.0%). (6.1)

To report SUSPECTED ADVERSE REACTIONS, contact Aimmune Therapeutics, Inc. at 1-833-246-2566 or FDA at 1-800-FDA-1088 or www.fda.gov/medwatch.

7 DRUG INTERACTIONS

Antibacterials should not be administered concurrently with VOWST. (7)

FULL PRESCRIBING INFORMATION

1 INDICATIONS AND USAGE

VOWST is indicated to prevent the recurrence of Clostridioides difficile infection (CDI) in individuals 18 years of age and older following antibacterial treatment for recurrent CDI (rCDI).

Limitation of Use:

VOWST is not indicated for treatment of CDI.

2 DOSAGE AND ADMINISTRATION

2.1 Prior to taking the first dose

- Complete antibacterial treatment for recurrent CDI 2 to 4 days before initiating treatment with VOWST.
- Drink 296 mL (10 oz) magnesium citrate, on the day before and at least 8 hours prior to taking the first dose of VOWST. In clinical studies, participants with impaired kidney function received polyethylene glycol electrolyte solution (250 mL GoLYTELY, not approved for this use) [see Clinical Studies (14)].
- Do not eat or drink, except for small amount of water, for at least 8 hours prior to taking the first dose.

2.2 Dosing regimen

- The dosage of VOWST is 4 capsules taken orally once daily for 3 consecutive days.
- Take each dose (4 capsules) on an empty stomach prior to the first meal of the day.

3 DOSAGE FORMS AND STRENGTHS

Capsule. A single dose is 4 capsules.

4 CONTRAINDICATIONS

None.

5 WARNINGS AND PRECAUTIONS

5.1 Transmissible infectious agents

Because VOWST is manufactured from human fecal matter, it may carry a risk of transmitting infectious agents. Any infection suspected by a healthcare provider possibly to have been transmitted by this product should be reported by the healthcare provider to Aimmune Therapeutics, Inc. at 1-833-246-2566.

5.2 Potential presence of food allergens

VOWST is manufactured from human fecal matter and may contain food allergens. The potential for VOWST to cause adverse reactions due to food allergens is unknown.

6 ADVERSE REACTIONS

The most common adverse reactions (reported in ≥5% of participants) were abdominal distension (31.1%), fatigue (22.2%), constipation (14.4%), chills (11.1%), and diarrhea (10.0%).

6.1 Clinical Trials Experience

Because clinical trials are conducted under widely varying conditions, adverse reaction rates observed in the clinical trials of a drug cannot be directly compared to rates in the clinical trials of another drug and may not reflect the rates observed in practice.

The safety of VOWST was evaluated in one Phase 3, randomized, double-blind clinical study (Study 1: NCT03183128) and one Phase 3, open-label clinical study (Study 2: NCT03183141) conducted in the United States and Canada. Adults with confirmed rCDI were required to have symptoms controlled 48 to 96 hours post-antibacterial treatment to be eligible for enrollment and randomization (1:1) to receive either VOWST or placebo (capsules containing 92 ± 4% glycerol in saline) for 3 consecutive days. Participants with neutropenia (absolute neutrophil count of <500 cells/mm^3), toxic megacolon, or small bowel ileus were excluded from these studies. A total of 349 adults 18 years of age and older with rCDI were exposed to VOWST across both Study 1 (n=90) and Study 2 (n=259). Across both Study 1 and Study 2, 99.1% of adults (346/349) received all scheduled doses of VOWST. Overall, across the 2 studies, the median age of VOWST recipients was 66 years (range, 21-100 years). The racial and ethnic distribution was as follows: 92.3% were white and 5.2% were black. In Study 1, females comprised 68.9% of the VOWST arm compared to 51.1% in the placebo arm. Rates of the following comorbidities (at study entry) were similar across the VOWST and placebo arms: cardiac disease (33.3% and 31.5%, respectively), immunocompromise/immunosuppression (28.9% and 30.4%, respectively), diabetes (20.0% and 27.2%, respectively), and renal impairment (14.4% and 15.2%, respectively). In Study 2, 68.4% were females and representation of comorbidities was similar to Study 1.

Adverse Reactions

In Study 1, participants recorded solicited adverse events in a diary for 7 days after completion of the 3-day regimen of VOWST or placebo. In both Study 1 and Study 2, participants were monitored for unsolicited adverse events by queries during weekly encounters for a period of 8 weeks. Monitoring for serious adverse events and adverse events of special interest (i.e., invasive infections) continued for a period of 6 months after the first dose of study drug. In Study 1, a multi-center, double-blind randomized (1:1), placebo-controlled trial conducted in the United States and Canada, adults 18 years of age and older (range: 18 to 100 years of age) received three daily doses of VOWST (n=90) or placebo (n=92). Overall through the 24 week follow up period, 12 VOWST recipients (13.3%) and 37 placebo recipients (40.2%) did not complete the study.

Participants with a recurrence of CDI during the first 8 weeks after receipt of first dose of VOWST or placebo were eligible to enroll into Study 2 and were no longer followed for safety in Study 1. During the first 8 weeks following VOWST or placebo, 5 participants (5.6%) and 28 participants (30.4%) respectively, did not complete 8 weeks of study participation. Of these, 4 VOWST recipients and 25 placebo recipients discontinued Study 1 and enrolled in Study 2.

In Study 1, within 8 weeks following VOWST or placebo, the most common solicited adverse reactions reported by ≥5% of VOWST recipients, and at a rate greater than that reported by placebo recipients, were abdominal distension (31.1%), fatigue (22.2%), constipation (14.4%), and chills (11.1%). The most common unsolicited adverse reaction was diarrhea (10.0%) (Table 1). The median duration (days) of these events was 5 days or less; specifically, abdominal distension (3.0), constipation (2.0), fatigue (4.5), chills (1.5), and diarrhea (5.0).

Table 1: Adverse Reactions Reported in ≥5% of VOWST-treated Participants and at a Frequency Greater than Placebo within 8 weeks after receipt of VOWST or placebo (Study 1) [Safety population, defined as all randomized participants who received a dose of study medication, by treatment received 85/90 participants in the VOWST group and 64/92 participants in the placebo group completed 8 week follow up.]
Adverse Reaction | VOWST N=90 % | Placebo N=92 %
Solicited [Solicited adverse events were recorded by participants in a diary for 7 days after completion of the 3-day regimen of VOWST or placebo. Participants were monitored for unsolicited events by queries during visits for a period of 8 weeks after the first dose of study drug.]
Abdominal distension | 31.1 | 29.3
Fatigue | 22.2 | 21.7
Constipation | 14.4 | 10.9
Chills | 11.1 | 7.6
Unsolicited
Diarrhea | 10.0 | 4.3
System Organ Class and Preferred Terms reported by Medical Dictionary for Regulatory Activities (MedDRA) version 20.0

In Study 1, most adverse reactions occurred within 10 days of starting treatment with VOWST. After this, the proportion of participants with adverse reactions declined through follow-up. The majority of adverse reactions were mild or moderate in severity.

In Study 2, the most commonly reported adverse reactions were preferred terms under the system organ class of Gastrointestinal disorders, namely flatulence (4.2%), diarrhea (3.4%) and nausea (3.0%). The majority of adverse reactions were mild to moderate in severity. All adverse events collected in Study 2 were unsolicited.

Serious Adverse Events

Among 349 VOWST recipients, there were no serious adverse events considered related to VOWST.

7 DRUG INTERACTIONS

VOWST contains bacterial spores; therefore, antibacterials should not be administered concurrently with VOWST.

8 USE IN SPECIFIC POPULATIONS

8.1 Pregnancy

Risk Summary

All pregnancies have a background risk of major birth defect, loss, or other adverse outcomes. In the U.S. general population, the estimated background risk of major birth defects and miscarriages in clinically recognized pregnancies is 2% to 4% and 15% to 20%, respectively.

There are no data on use of VOWST in pregnant individuals. Developmental toxicity studies in animals have not been conducted with VOWST.

8.2 Lactation

Risk Summary

It is not known whether VOWST is excreted in human milk. Data are not available to assess the effects of VOWST on the breastfed infant or on milk production/excretion.The developmental and health benefits of breastfeeding should be considered, along with the mother's clinical need for VOWST and any other potential adverse effects on the breastfed child from VOWST or from the underlying maternal condition.

8.4 Pediatric Use

The safety and effectiveness of VOWST in individuals younger than 18 years of age have not been established.

8.5 Geriatric Use

Of the 349 adults who received VOWST, 52.4% were 65 years of age and over (n=183), and 28.1% were 75 years of age and over (n=98). Data from clinical studies of VOWST are not sufficient to determine if adults 65 years of age and older respond differently than younger adults.

11 DESCRIPTION

VOWST (fecal microbiota spores, live-brpk) is a bacterial spore suspension in capsules for oral administration. VOWST is manufactured from human fecal matter sourced from qualified donors. Human fecal matter donations are routinely tested for a panel of transmissible pathogens. Donors do not have dietary restrictions with respect to potential food allergens. The spore suspension is generated by treating fecal matter with ethanol to kill organisms that are not spores, followed by filtration steps to remove solids and residual ethanol. Each capsule of VOWST contains between 1×10^6 and 3×10^7 Firmicutes spore colony forming units in 92 ± 4% (w/w) glycerol in saline.

12 CLINICAL PHARMACOLOGY

12.1 Mechanism of Action

The mechanism of action of VOWST has not been established.

13 NONCLINICAL TOXICOLOGY

13.1 Carcinogenesis, Mutagenesis, Impairment of Fertility

VOWST has not been evaluated for carcinogenicity, genotoxicity, mutagenic potential, or impairment of male or female fertility in animals.

14 CLINICAL STUDIES

The efficacy of VOWST was evaluated in a randomized placebo-controlled multi-center study (Study 1). The primary objective was to demonstrate the reduction of CDI recurrence with VOWST. Enrolled participants were 18 years of age or older and had a confirmed diagnosis of recurrent CDI (with a total of ≥3 episodes of CDI within 12 months). CDI episode at the study entry was defined as diarrhea (≥3 unformed stools per day for at least 2 consecutive days) and a positive C. difficile stool sample using a toxin assay. Participants were required to have symptom resolution, defined as <3 unformed stools in 24 hours for 2 or more consecutive days prior to randomization, following 10 to 21 days of standard-of-care antibacterial treatment with vancomycin or fidaxomicin. Participants were stratified by antibacterial received (vancomycin or fidaxomicin) and age (<65 years or ≥65 years) and randomized 1:1 to receive a dose of VOWST or placebo once daily for 3 consecutive days. The day prior to starting the assigned treatment regimen, participants were required to drink 296 mL (10 oz) of magnesium citrate or based on medical judgment, 250 mL polyethylene glycol electrolyte solution (GoLYTELY, not approved for this use). Participants with impaired kidney function who were unable to take magnesium citrate took 250 mL polyethylene glycol electrolyte solution. All participants fasted for at least 8 hours before taking the first dose of VOWST. Participants were also required to continue fasting for 1 hour after the first day of treatment with VOWST. For Days 2 and 3, VOWST was taken in the morning before breakfast.

In the intent-to-treat population consisting of all 182 randomized participants, 89 were in the VOWST group and 93 were in the placebo group. The participants had a mean age of 65.5 years (range, 18–100 years), 93.4% were white, 59.9% were female, and 73.1% received vancomycin.

The primary efficacy endpoint was CDI recurrence through 8 weeks after completion of treatment. Participants were assessed for recurrence, which was defined as ≥3 unformed stools per day for 2 consecutive days with continued diarrhea until antibacterial treatment was initiated, a positive C. difficile test on a stool sample determined by a toxin assay, and assessment by the Investigator that the clinical condition of the participant warranted antibacterial treatment.

Through 8 weeks after treatment, CDI recurrence in VOWST-treated participants was lower compared to that in placebo-treated participants (12.4% compared to 39.8%). VOWST met the pre-specified success criterion of the upper bound of the two-sided 95% confidence interval of the CDI relative risk lower than 0.83 (see Table 2).

Table 2: Efficacy Results through 8 Weeks after VOWST Treatment (Study 1, Intent-to-Treat Population [Intent-to-treat population, consisted of all participants who were randomized. Participants were analyzed according to randomized treatment assignment which differed from actual treatment received for 5 participants (3 participants randomized to placebo received VOWST and 2 participants randomized to VOWST received placebo), which resulted in differing number of participants in each treatment arm for efficacy and safety analyses.])
 | VOWST N=89 n (%) | Placebo N=93 n (%) | Relative Risk (95% CI) [VOWST divided by Placebo recurrence rate adjusted for stratification based on Cochran-Mantel-Haenszel method. 95% CI based on Greenland-Robins method. VOWST met the pre-specified success criterion of the upper bound of the two-sided 95% CI of the CDI relative risk <0.83.]
CDI Recurrence [Participants who were lost to follow-up, terminated the study prematurely, or died without a recorded recurrence before the end of the time interval (1 and 2 participants in VOWST and placebo group, respectively) were assumed to have had a recurrence.] | 11 (12.4) | 37 (39.8) | 0.32 (0.18; 0.58)
CDI=C. difficile infection; CI=confidence interval; n (%)=Number (percentage) of participants in the analysis population meeting the criteria for endpoint; N = Number of participants included in the analysis population

Through 12 weeks after treatment, the recurrence rates for VOWST and placebo recipients were 18.0% (16/89) and 46.2% (43/93), respectively with a relative risk of 0.40 (95% CI 0.24,0.65). Through 24 weeks after treatment, recurrence rates for VOWST and placebo recipients were 21.3% (19/89) and 47.3% (44/93), respectively with a relative risk of 0.46 (95% CI 0.30, 0.73).

16 HOW SUPPLIED/STORAGE AND HANDLING

VOWST is supplied as capsules in bottles with child-resistant caps. Each bottle contains 12 white capsules imprinted with "SER109". Each bottle is supplied in a carton.

Bottles of 12 capsules: NDC 71881-400-12.

STORAGE AND HANDLING

Store VOWST in the original packaging at 2° to 25°C (36° to 77°F). Do not store in the freezer.

17 PATIENT COUNSELING INFORMATION

Advise the patient to read the FDA-approved patient labeling (Patient Information).

Inform patients not to take VOWST concurrently with antibacterials [see Drug Interactions (7)].

Distributed by:
Aimmune Therapeutics, Inc.
1007 US Highway 202/206, Bridgewater, NJ 08807
US license number: 2109

VOWST is a trademark of Société des Produits Nestlé S.A.,
Vevey, Switzerland. © 2025 Nestlé.

GoLYTELY is a registered trademark of Braintree Laboratories, Inc.

Patient Information
VOWST (pronounced Vowst)
(fecal microbiota spores, live – brpk)
capsules, for oral use

Before you take VOWST, read this information sheet and be sure you understand it. If you have questions or experience any side effects, talk to your healthcare provider. This information does not take the place of talking about VOWST with your healthcare provider. Keep this patient information so you can read it again.

What is VOWST?
VOWST is a prescription medicine used to prevent Clostridioides difficile (C. difficile) infection from coming back in people 18 years of age or older after antibiotic treatment for C. difficile infection has been completed.
VOWST is not intended for treatment of C. difficile infection.

How should I take VOWST?

- VOWST is taken over three consecutive days.
- Before you take VOWST:
  - 2 to 4 days before your first dose of VOWST, finish your antibiotic treatment for C. difficile infection.
  - On the day before and at least 8 hours prior to the first dose of VOWST, drink 10 oz (296 mL) of magnesium citrate laxative.
  - Do not eat or drink, except for small amount of water, for at least 8 hours prior to taking the first dose.
- The next day after taking the laxative, take 4 VOWST capsules by mouth on an empty stomach prior to the first meal of the day.
- Take 4 VOWST capsules by mouth once daily for two more days in a row. Take VOWST capsules on an empty stomach prior to the first meal of the day.

Swallow each capsule whole. DO NOT crush, chew, or break the capsules.

Do any medications interfere with VOWST?
VOWST contains live bacteria. Antibiotics can interfere with VOWST. VOWST should not be taken at the same time as antibiotics.

What should I tell my healthcare provider before taking VOWST?
Tell your healthcare provider if you:

- have kidney disease because you may not be able to take the magnesium citrate laxative.
- have any other medical conditions now or have had before.
- take any medicines, including prescription and over-the-counter medicines, vitamins, and supplements.
- are pregnant or planning to get pregnant.
- are breast-feeding.

What are the possible side effects of VOWST?
The most common side effects observed in patients taking VOWST were:

- bloated abdomen
- fatigue
- constipation
- chills
- diarrhea

These are not all the possible side effects of VOWST. Be sure to tell your healthcare provider about any side effect that bothers you or that does not go away. For more information, ask your healthcare provider or pharmacist.
Call your healthcare provider for medical advice about side effects. You may report side effects to Aimmune Therapeutics, Inc. at 1-833-246-2566 or FDA at 1-800-FDA-1088 or report online to www.fda.gov/medwatch.

How should I store VOWST?

- Keep the bottle of VOWST capsules either in the refrigerator or at room temperature (36 to 77°F, 2 to 25°C). Do not store in the freezer.
- Do not use VOWST past the expiration date stamped on the carton and the bottle.

Keep VOWST out of the reach of children.

What if I have questions?

- Call your healthcare provider.
- Call Aimmune Therapeutics, Inc.at 1-833-AIM-2KNO (1-833-246-2566).
- Go to the website www.VOWST.com.

What are the ingredients in VOWST?
Active ingredient: live bacterial spores
Inactive ingredients: Glycerol, Saline

Distributed by:
Aimmune Therapeutics, Inc.
1007 US Highway 202/206, Bridgewater, NJ 08807
US license number: 2109
VOWST is a trademark of Société des Produits Nestlé S.A.,
Vevey, Switzerland. © 2025 Nestlé.

This Patient Information has been approved by the U.S. Food and Drug Administration.
Issued 02/2025

PRINCIPAL DISPLAY PANEL - 12 Capsule Bottle Carton

fecal microbiota
spores, live-brpk
VOWST®

Contents: One bottle containing 12 capsules

Distributed by Aimmune Therapeutics, Inc.

NDC 71881-400-12

Rx Only